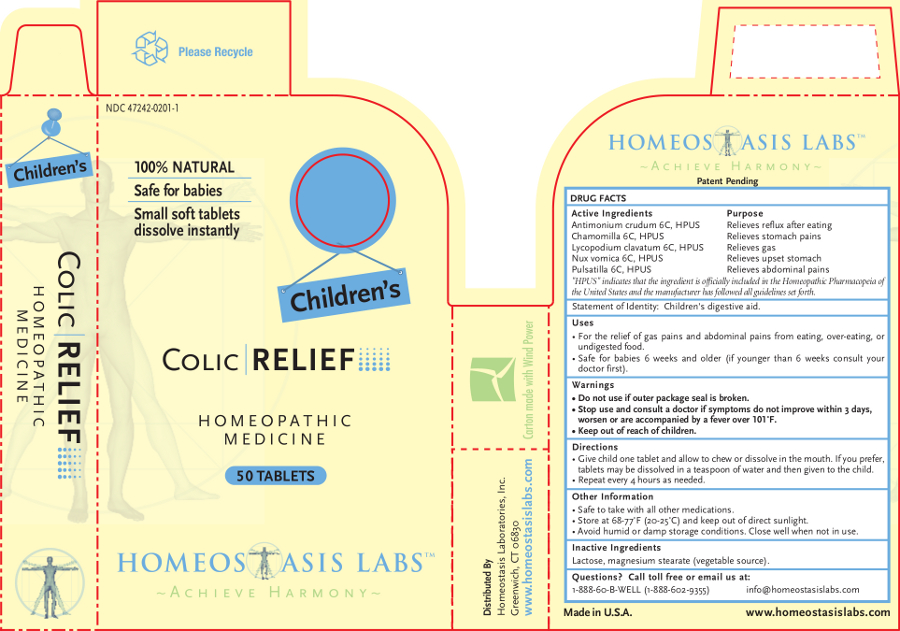 DRUG LABEL: Childrens Colic RELIEF
NDC: 47242-0201 | Form: TABLET, CHEWABLE
Manufacturer: Homeostasis Laboratories, Inc.
Category: homeopathic | Type: HUMAN OTC DRUG LABEL
Date: 20121114

ACTIVE INGREDIENTS: ANTIMONY TRISULFIDE 6 [hp_C]/1 1; MATRICARIA RECUTITA 6 [hp_C]/1 1; STRYCHNOS NUX-VOMICA SEED 6 [hp_C]/1 1; LYCOPODIUM CLAVATUM SPORE 6 [hp_C]/1 1; PULSATILLA VULGARIS 6 [hp_C]/1 1
INACTIVE INGREDIENTS: LACTOSE; MAGNESIUM STEARATE

Children's Colic RELIEF

Active Ingredients | Purpose
Antimonium crudum 6C, HPUS | Relieves reflux after eating
Chamomilla 6C, HPUS | Relieves stomach pains
Lycopodium Clavatum 6C, HPUS | Relieves gas
Nux vomica 6C, HPUS 6C, HPUS | Relieves upset stomach
Pulsatilla 6C, HPUS | Relieves abdominal pains

"HPUS" indicates that the ingredient is officially included in the Homeopathic Pharmacopeia of the United States and the manufacturer has followed all guidelines set forth.

Statement of Identity: Children's digestive aid.

Uses

For the relief of gas pains and abdominal pains from eating, over-eating, or undigested food.

Safe for babies 6 weeks and older (if younger than 6 weeks consult your doctor first).

Warnings

- Do not use if outer package seal is broken.
- Stop use and consult a doctor if symptoms do not improve within 3 days, worsen or are accompanied by a fever over 101˚F.

- Keep out of reach of children.

Directions

Give child one tablet and allow to chew or dissolve in the mouth. If you prefer, tablets may be dissolved in a teaspoon of water and then given to the child.

Repeat every 4 hours as needed.

Other information

- Safe to take with all other medications.
- Store at 68-77°F (20-25°C) and keep out of direct sunlight.
- Avoid humid or damp storage conditions. Close well when not in use.

Inactive Ingredients

Lactose, magnesium stearate (vegetable source).

Questions? Call toll free or email us at:

1-888-60-B-WELL (1-888-602-9355)

info@homeostasislabs.com